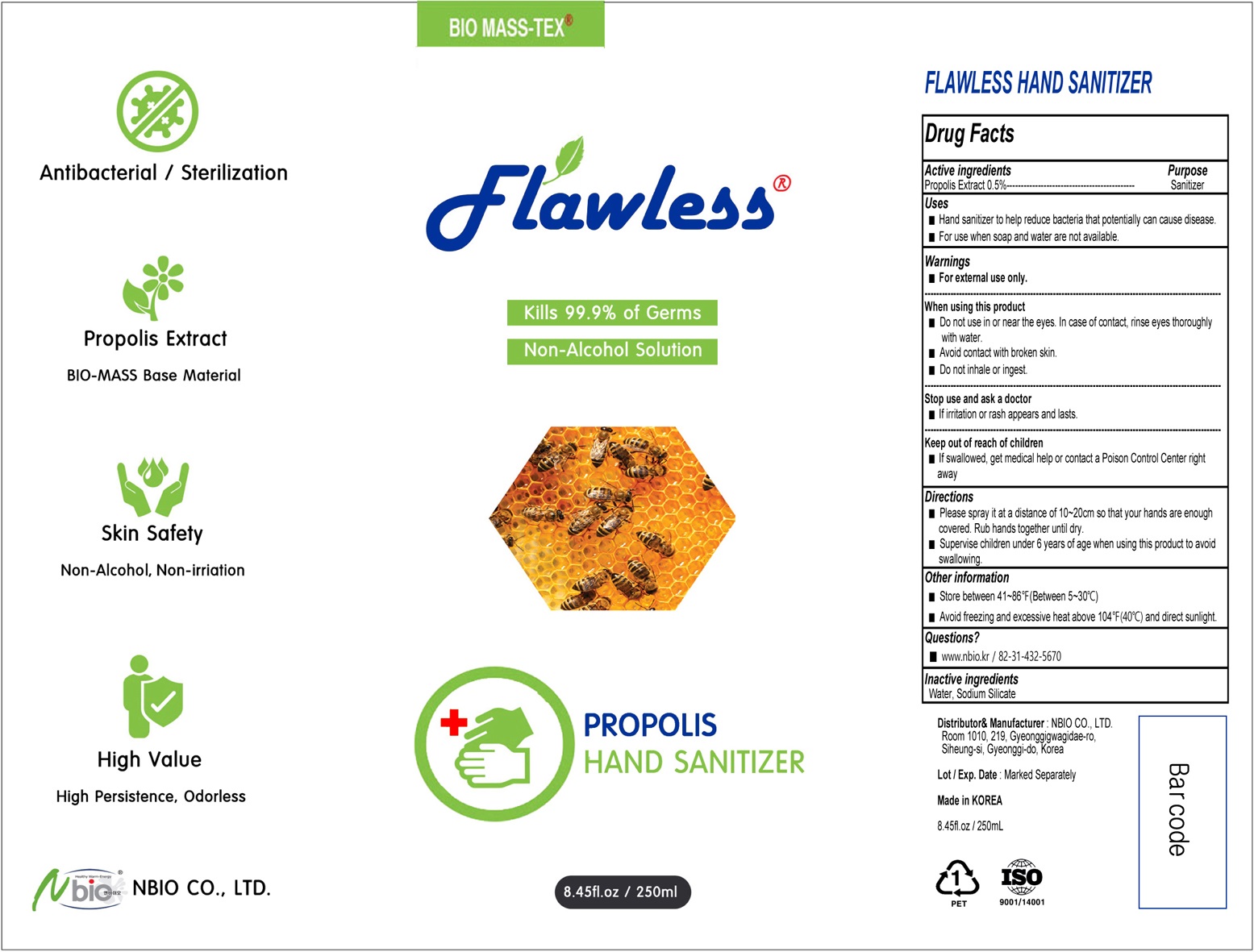 DRUG LABEL: FLAWLESS HAND SANITIZER
NDC: 77560-010 | Form: SPRAY
Manufacturer: NBIO CO., LTD.
Category: otc | Type: HUMAN OTC DRUG LABEL
Date: 20200515

ACTIVE INGREDIENTS: PROPOLIS WAX 1.25 g/250 mL
INACTIVE INGREDIENTS: Water; Sodium Silicate

ACTIVE INGREDIENT

Propolis Extract 0.5%

INACTIVE INGREDIENTS

Water, Sodium Silicate

PURPOSE

Sanitizer

WARNINGS

■ For external use only.
--------------------------------------------------------------------------------------------------------
When using this product
■ Do not use in or near the eyes. In case of contact, rinse eyes thoroughly
with water.
■ Avoid contact with broken skin.
■ Do not inhale or ingest.
--------------------------------------------------------------------------------------------------------
Stop use and ask a doctor
■ If irritation or rash appears and lasts.

KEEP OUT OF REACH OF CHILDREN

■ If swallowed, get medical help or contact a Poison Control Center right away

Uses

■ Hand sanitizer to help reduce bacteria that potentially can cause disease.
■ For use when soap and water are not available.

Directions

■ Please spray it at a distance of 10~20cm so that your hands are enough covered. Rub hands together until dry.
■ Supervise children under 6 years of age when using this product to avoid swallowing.

Other information

■ Store between 41~86℉(Between 5~30℃)
■ Avoid freezing and excessive heat above 104℉(40℃) and direct sunlight.

QUESTIONS

■ www.nbio.kr / 82-31-432-5670